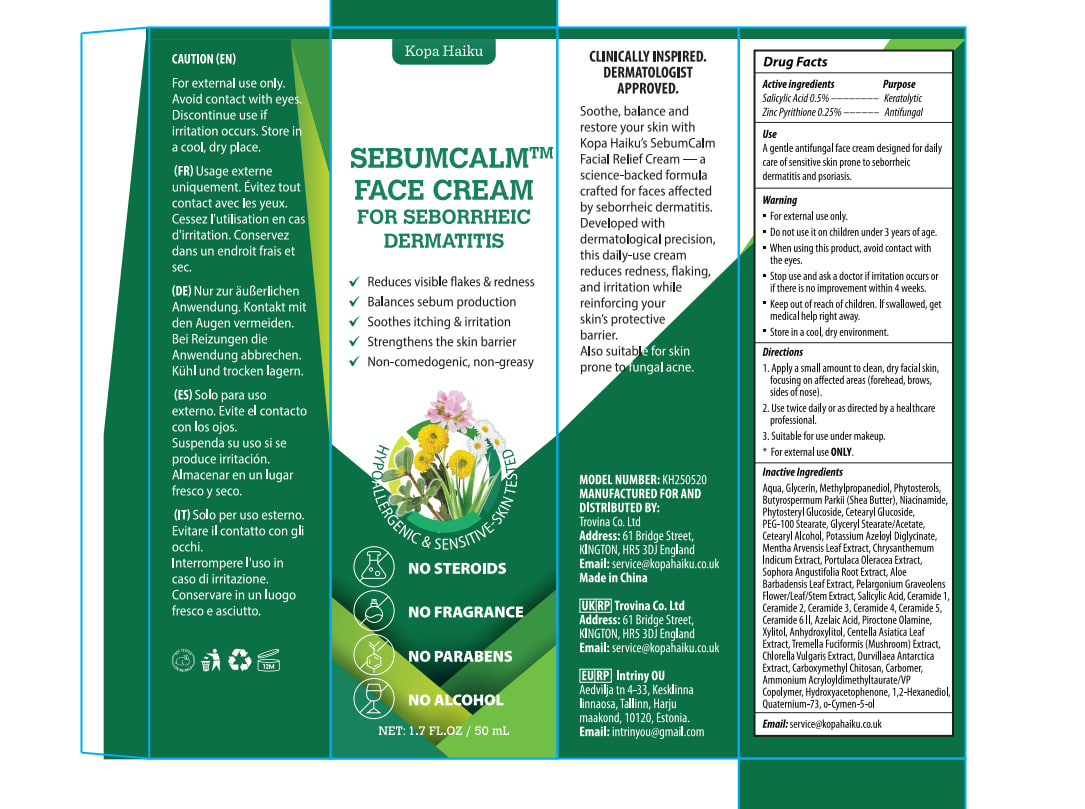 DRUG LABEL: Kopa Haiku Seborrheic Dermatitis Face Cream
NDC: 87041-005 | Form: CREAM
Manufacturer: Trovina Co. Ltd
Category: otc | Type: HUMAN OTC DRUG LABEL
Date: 20260212

ACTIVE INGREDIENTS: ZINC PYRITHIONE 2.5 mg/1 g; SALICYLIC ACID 5 mg/1 g
INACTIVE INGREDIENTS: AQUA; NIACINAMIDE; HYDROXYACETOPHENONE; DURVILLAEA ANTARCTICA; CETEARYL GLUCOSIDE; CERAMIDE 3; CERAMIDE 4; PIROCTONE OLAMINE; POTASSIUM AZELOYL DIGLYCINATE; CERAMIDE 5; CERAMIDE 6 II; PELARGONIUM GRAVEOLENS FLOWERING TOP; BETA-SITOSTEROL; SHEA BUTTER; CETEARYL ALCOHOL; SITOGLUSIDE; CARBOMER HOMOPOLYMER TYPE C; ACETOMONOSTEARIN; QUATERNIUM-73; O-CYMEN-5-OL; N-CARBOXYMETHYLCHITOSAN; PORTULACA OLERACEA WHOLE; XYLITOL; TREMELLA FUCIFORMIS WHOLE; 1,2-HEXANEDIOL; CERAMIDE 1; GLYCERIN; AMMONIUM ACRYLOYLDIMETHYLTAURATE/VP COPOLYMER; ALOE VERA LEAF; METHYLPROPANEDIOL; CHRYSANTHELLUM INDICUM WHOLE; SOPHORA FLAVESCENS ROOT; AZELAIC ACID; ANHYDROXYLITOL; CENTELLA ASIATICA LEAF; CERAMIDE 2; MENTHA ARVENSIS LEAF; CHLORELLA VULGARIS; PEG-100 STEARATE

ACTIVE INGREDIENT

Salicylic Acid 0.5% and Zinc Pyrithione 0.25%

PURPOSE

Keratolytic and Antifungal

INDICATIONS AND USAGE

A gentle antifungal face cream designed for daily care of sensitive skin prone to seborrheic dermatitis and psoriasis.

WARNINGS

For external use only.

Do not use it on children under 3 years of age.

OTHER SAFETY INFORMATION

Avoid contact with the eyes.

STOP USE

Irritation occurs or if there is no improvement within 4 weeks.

Keep out of reach of children. In case of ingestion, seek medical help or contact a Poison Control Center immediately.

DOSAGE AND ADMINISTRATION

1. Apply a small amount to clean, dry facial skin, focusing on affected areas (forehead, brows, sides of nose). 2. Use twice daily or as directed by a healthcare professional. 3. Suitable for use under makeup.4. For external use only.

STORAGE AND HANDLING

Store in a cool, dry environment.

INACTIVE INGREDIENT

AUQA,

GLYCERIN,

METHYLPROPANEDIOL,

PHYTOSTEROLS,

BUTYROSPERMUM PARKII (SHEA BUTTER),

NIACINAMIDE,

PHYTOSTERYL GLUCOSIDE,

CETEARYL GLUCOSIDE,

PEG-100 STEARATE,

GLYCERYL STEARATE/ACETATE,

CETEARYL ALCOHOL,

POTASSIUM AZELOYL DIGLYCINATE,

AZELAIC ACID,

MENTHA ARVENSIS LEAF EXTRACT,

CHRYSANTHELLUM INDICUM EXTRACT,

PORTULACA OLERACEA EXTRACT,

SOPHORA ANGUSTIFOLIA ROOT EXTRACT,

ALOE BARBADENSIS LEAF EXTRACT,

PELARGONIUM GRAVEOLENS FLOWER/LEAF/STEM EXTRACT,

CERAMIDE 1,

CERAMIDE 2,

CERAMIDE 3,

CERAMIDE 4,

CERAMIDE 5,

CERAMIDE 6 II,

PIROCTONE OLAMINE,

SALICYLIC ACID,

XYLITOL,

ANHYDROXYLITOL,

CENTELLA ASIATICA LEAF EXTRACT,

TREMELLA FUCIFORMIS (MUSHROOM) EXTRACT,

CHLORELLA VULGARIS EXTRACT,

DURVILLEA ANTARTICA EXTRACT,

CARBOXYMETHYL CHITOSAN,

CARBOMER,

AMMONIUM ACRYLOYLDIMETHYLTAURATE/VP COPOLYMER,

HYDROXYACETOPHENONE,

1,2-HEXANEDIOL,

QUATERNIUM-73,

o-CYMEN-5-OL,

QUESTIONS

Email at: service@kopahaiku.co.uk